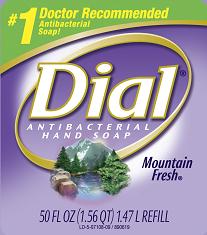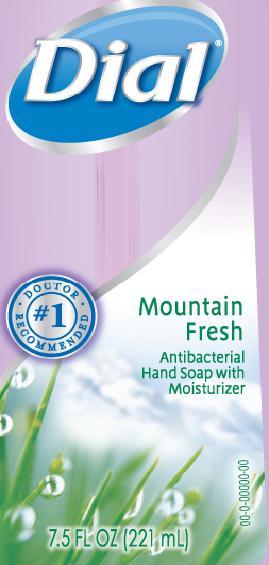 DRUG LABEL: Dial Mountain Fresh Antibacterial Soap
NDC: 54340-801 | Form: SOLUTION
Manufacturer: The Dial Corporation
Category: otc | Type: HUMAN OTC DRUG LABEL
Date: 20100122

ACTIVE INGREDIENTS: TRICLOSAN 0.15 mL/1000 mL

Drug Facts

Active Ingredient - TRICLOSAN 0.15%

Purpose - Antibacterial

PURPOSE

Uses - For handwashing to decrease bacteria on the skin

Warnings - For external use only

When using this product avoid contact with eyes. In case of eye contact, flush with water.

Stop use and ask a doctor if irritation and redness develops.

Keep out of reach of children. If swallowed, get medical help or contact a Poison Control Center right away.

Directions: Pump into hands, wet as needed. Lather vigorously for at lest 15 seconds. Wash skin, rinse thoroughly and dry.

INACTIVE INGREDIENT

Inactive Ingredients:Water, Sodium Laureth Sulfate, Decyl Glucoside, Cocamidopropyl Betaine, Sodium Chloride, Cocamide MEA, Fragrance, PEG-120 Methyl Glucose Dioleate, PEG-18, Glyceryl Oleate/Cocate Aloe-Barbadensis Leaf Juice, Polyquaternium-7, DMDM Hydantoin, Tetrasodium EDTA, Citric Acid, Red 33, Blue1

Questions? 1-800-258-DIAL (3425)